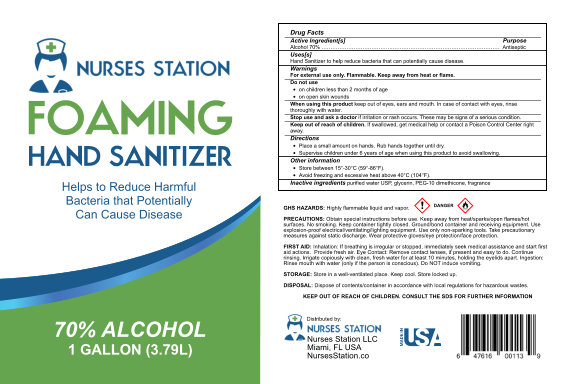 DRUG LABEL: Hand Sanitizer
NDC: 75009-172 | Form: LIQUID
Manufacturer: Alpha Aromatics
Category: otc | Type: HUMAN OTC DRUG LABEL
Date: 20220121

ACTIVE INGREDIENTS: ALCOHOL 70 mL/100 mL
INACTIVE INGREDIENTS: GLYCERIN 0.5 mL/100 mL; DIMETHICONE 200; WATER; LINALOOL, (+)- 0.002 mL/100 mL; CYCLAMEN ALDEHYDE 0.004 mL/100 mL

CUCUMER FOAMING HAND SANITIZER 70%

Active Ingredient(s)

Alcohol 70% v/v. Purpose: Antiseptic

Purpose

Antiseptic, Hand Sanitizer

Use

Hand Sanitizer to help reduce bacteria that potentially can cause disease. For use when soap and water are not available.

Warnings

For external use only. Flammable. Keep away from heat or flame

Do not use

- in children less than 2 months of age
- on open skin wounds

When using this product keep out of eyes, ears, and mouth. In case of contact with eyes, rinse eyes thoroughly with water.
Stop use and ask a doctor if irritation or rash occurs. These may be signs of a serious condition.
Keep out of reach of children. If swallowed, get medical help or contact a Poison Control Center right away.

Stop use and ask a doctor if irritation or rash occurs. These may be signs of a serious condition.

Keep out of reach of children. If swallowed, get medical help or contact a Poison Control Center right away.

Directions

- Place a small amount on hands. Rub hands together until dry.
- Supervise children under 6 years of age when using this product to avoid swallowing.

Other information

- Store between 15-30C (59-86F)
- Avoid freezing and excessive heat above 40C (104F)

Inactive ingredients

purified water USP, glycerine, PEG-10 dimethicone, fragrance

Package Label - Principal Display Panel

3790 mL NDC: 75009-172-01